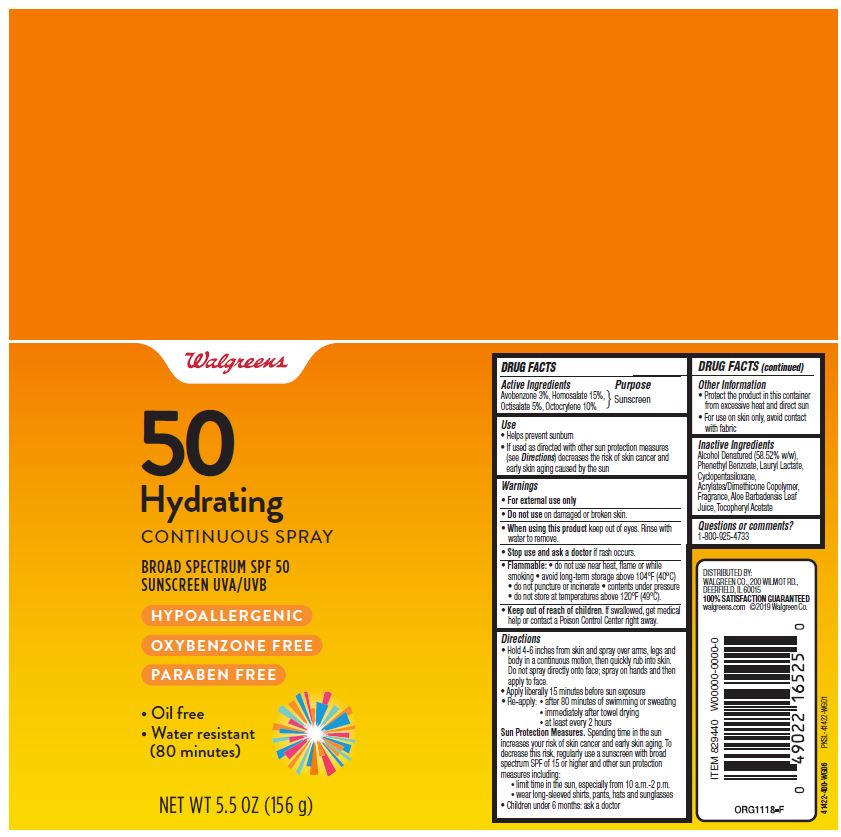 DRUG LABEL: WALG SUN MOIST SPF50
NDC: 0363-8227 | Form: SPRAY
Manufacturer: Walgreen Company
Category: otc | Type: HUMAN OTC DRUG LABEL
Date: 20190627

ACTIVE INGREDIENTS: HOMOSALATE 15 g/100 g; AVOBENZONE 3 g/100 g; OCTISALATE 5 g/100 g; OCTOCRYLENE 10 g/100 g
INACTIVE INGREDIENTS: ALOE VERA LEAF; DIMETHICONE CROSSPOLYMER (450000 MPA.S AT 12% IN CYCLOPENTASILOXANE); ALCOHOL; PHENETHYL BENZOATE; LAURYL LACTATE; ALPHA-TOCOPHEROL ACETATE

WALG SUN MOIST SPR SPF50 5.5OZ

Active Ingredients

Avobenzone 3%

Homosalate 15%

Octisalate 5%

Octocrylene 10%

Purpose

Sunscreen

Use

• Helps prevent sunburn • If used as directed with other sun

protection measures (see Directions) decreases the risk of skin

cancer and early skin aging caused by the sun

Warnings

• For external use only

• Do not use on damaged or broken skin.

• When using this product keep out of eyes. Rinse with water to

remove.

• Stop use and ask a doctor if rash occurs.

• Keep out of reach of children. If swallowed, get medical help or

contact a Poison Control Center right away.

Directions

• Apply liberally 15 minutes before sun exposure

• Re-apply: • after 80 minutes of swimming or sweating

• immediately after towel drying

• at least every 2 hours

Sun Protection Measures. Spending time in the sun increases your

risk of skin cancer and early skin aging. To decrease this risk,

regularly use a sunscreen with broad spectrum SPF of 15 or higher

and other sun protection measures including:

• limit time in the sun, especially from 10 a.m.-2 p.m.

• wear long-sleeved shirts, pants, hats and sunglasses

• Children under 6 months: ask a doctor

Other Information

• Protect the product in this container from excessive heat and direct sun

• For use on skin only, avoid contact with fabric

Inactive Ingredients

Alcohol Denatured (58.52% W/W), Phenethyl

Benzoate, Lauryl Lactate, Cyclopentasiloxane,

Acrylates/Dimethicone Copolymer, Fragrance, Aloe

Barbadensis Leaf Juice, Tocopheryl Acetate

Questions or comments?

1-800-925-4733

DISTRIBUTED BY:

WALGREEN CO.

200 WILMOT RD.,

DEERFIELD, IL 60015

100% SATISFACTION

GUARANTEED

walgreens.com

©2018 Walgreen Co

Principal Display Panel

Walgreens

50

Hydrating

CONTINUOUS SPRAY

Broad Spectrum SPF 50

Sunscreen UVA/UVB

HYPOALLERGENIC

OXYBENZONE FREE

PARABEN FREE

Oil free

Water resistant

(80 minutes)

NET WT. 5.5 OZ (156 g)